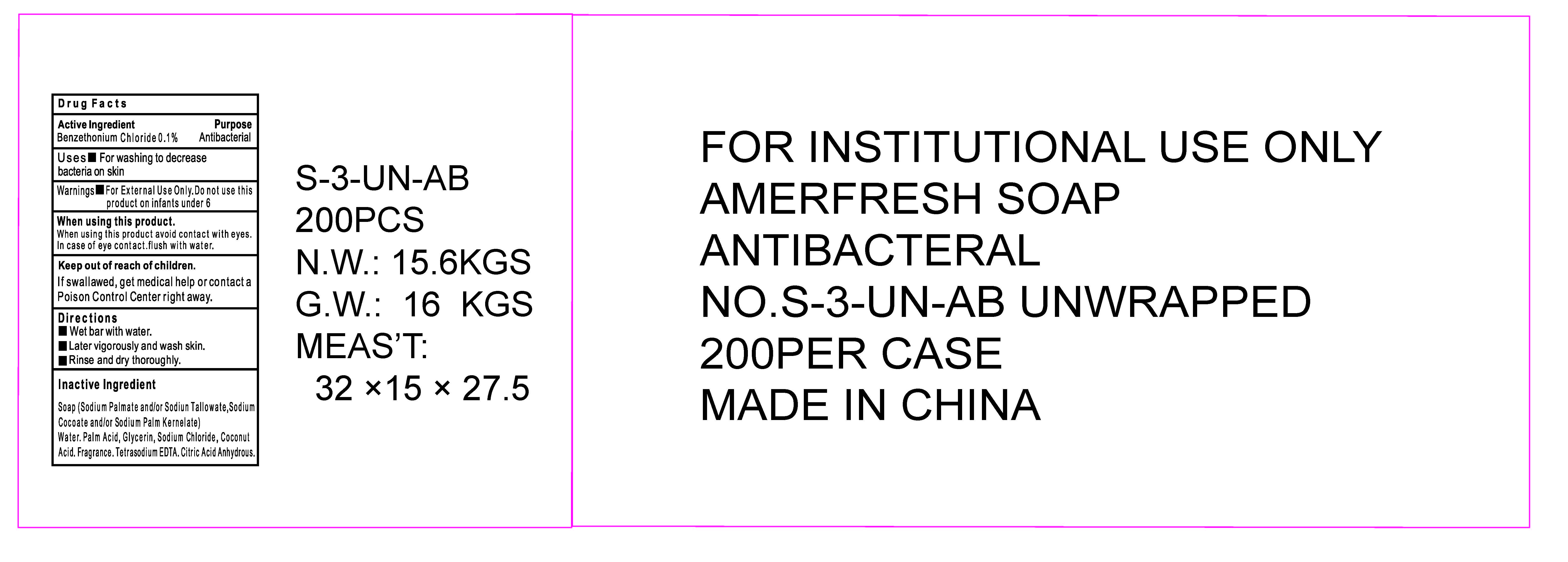 DRUG LABEL: AMERFRESH  Antibacterial
NDC: 73343-004 | Form: SOAP
Manufacturer: Yangzhou Tracey Daily Chemical Plastic Co., Ltd.
Category: otc | Type: HUMAN OTC DRUG LABEL
Date: 20200816

ACTIVE INGREDIENTS: BENZETHONIUM CHLORIDE 0.1 g/100 g
INACTIVE INGREDIENTS: SODIUM PALMATE; COCONUT ACID; PALM ACID; SODIUM PALM KERNELATE; DITETRACYCLINE TETRASODIUM EDETATE; WATER; GLYCERIN; SODIUM CHLORIDE; ANHYDROUS CITRIC ACID

73343 004 AMERFRESH Antibacterial SOAP (0.1%Benzethonium chloride)

Drug Facts

Active Ingredient

Benzethonium Chloride 0.1%

Purpose

Antibacterial

Uses

For washing to decrease bacteria on skin.

Warnings

For External Use Only.

When using this product avoid contact with eyes. In case of eye contact, flush with water.

Do not use this product on infants under 6.

Keep out of reach of children.

If swallowed, get medical help or contact a Poison Control Center right away.

Directions

- Wet bar with water
- Lather vigorously and wash skin
- Rinse and dry thoroughly

Inactive Ingredients

Soap (Sodium Palmate and/or Sodiun Tallowate. Sodium Cocoate and/or Sodium Palm Kernelate) Water, Palm Acid, Glycerin, Sodium Chloride, Coconut Acid,Fragrance, Tetrasodium EDTA, Citric Acid Anhydrous.